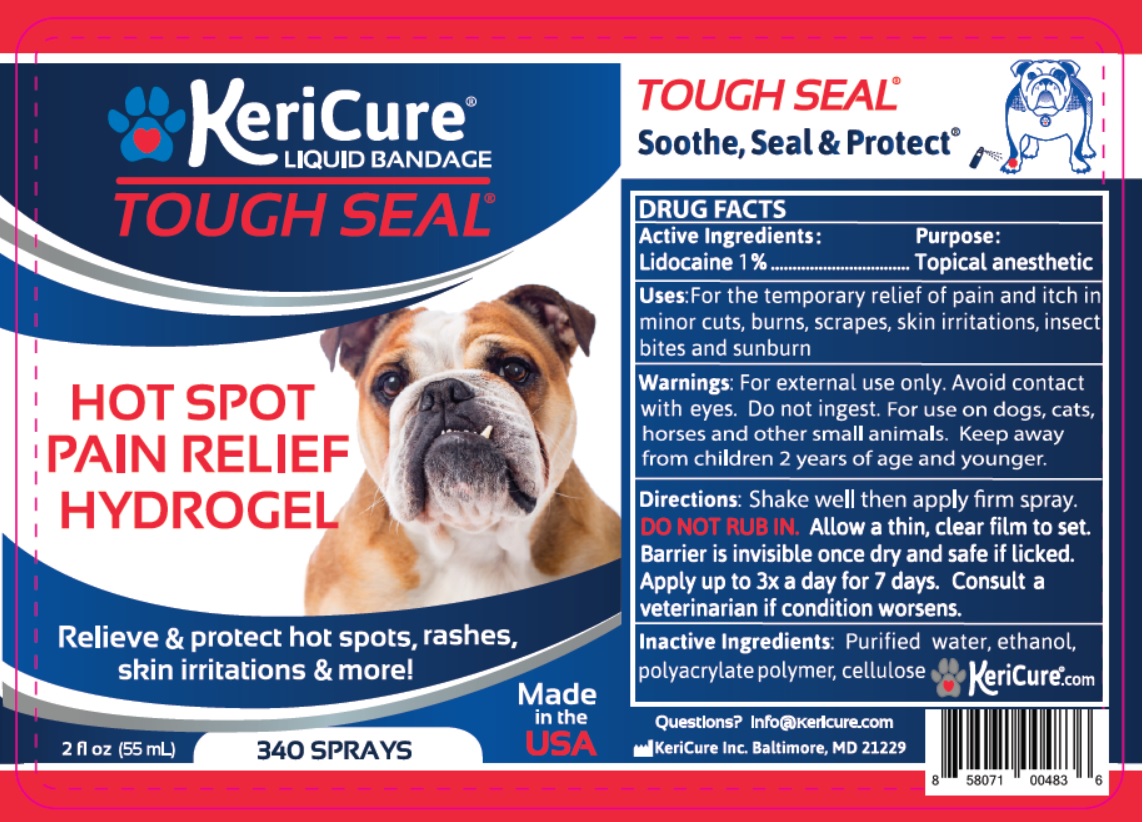 DRUG LABEL: Tough Seal Hot Spot plus Pain Relief
NDC: 78280-702 | Form: SPRAY
Manufacturer: Kericure Inc.
Category: animal | Type: OTC ANIMAL DRUG LABEL
Date: 20200601

ACTIVE INGREDIENTS: LIDOCAINE 10 mg/1 mL
INACTIVE INGREDIENTS: WATER; ALCOHOL; BUTYL ACRYLATE/METHYL METHACRYLATE/METHACRYLIC ACID COPOLYMER (18000 MW); HYDROXYETHYL CELLULOSE (2000 MPA.S AT 1%)

KeriCure® LIQUID BANDAGE TOUGH SEAL®

Active Ingredients:

Lidocaine 1%

Purpose:

Topical anasthetic

INDICATIONS AND USAGE

Uses: For the temporary relief of pain and itch in minor cuts, burns, scrapes, skin irritations, insect bites and sunburn

WARNINGS

Warnings: For external use only. Avoid contact with eyes. Do not ingest. For use on dogs, cats, horses and other small animals.

KEEP OUT OF REACH OF CHILDREN

Keep away from children 2 years of age and younger.

DOSAGE AND ADMINISTRATION

Directions: Shake well then apply firm spray.

DO NOT RUB IN. Allow a thin, clear film to set. Barrier is invisible once dry and safe if licked. Apply up to 3x a day for 7 days. Consult a veterinarian if condition worsens.

INACTIVE INGREDIENT

Inactive Ingredients: Purified water, ethanol, polyacrylate polymer, cellulose

HOT SPOT PAIN RELIEF HYDROGEL

Relieve & protect hot spots, rashes, skin irritations & more!

340 SPRAYS

Made in the USA

TOUGH SEAL®

Soothe, Seal & Protect®

Questions? info@Kericure.com

Kericure Inc. Baltimore, MD 21229

KeriCure®.com